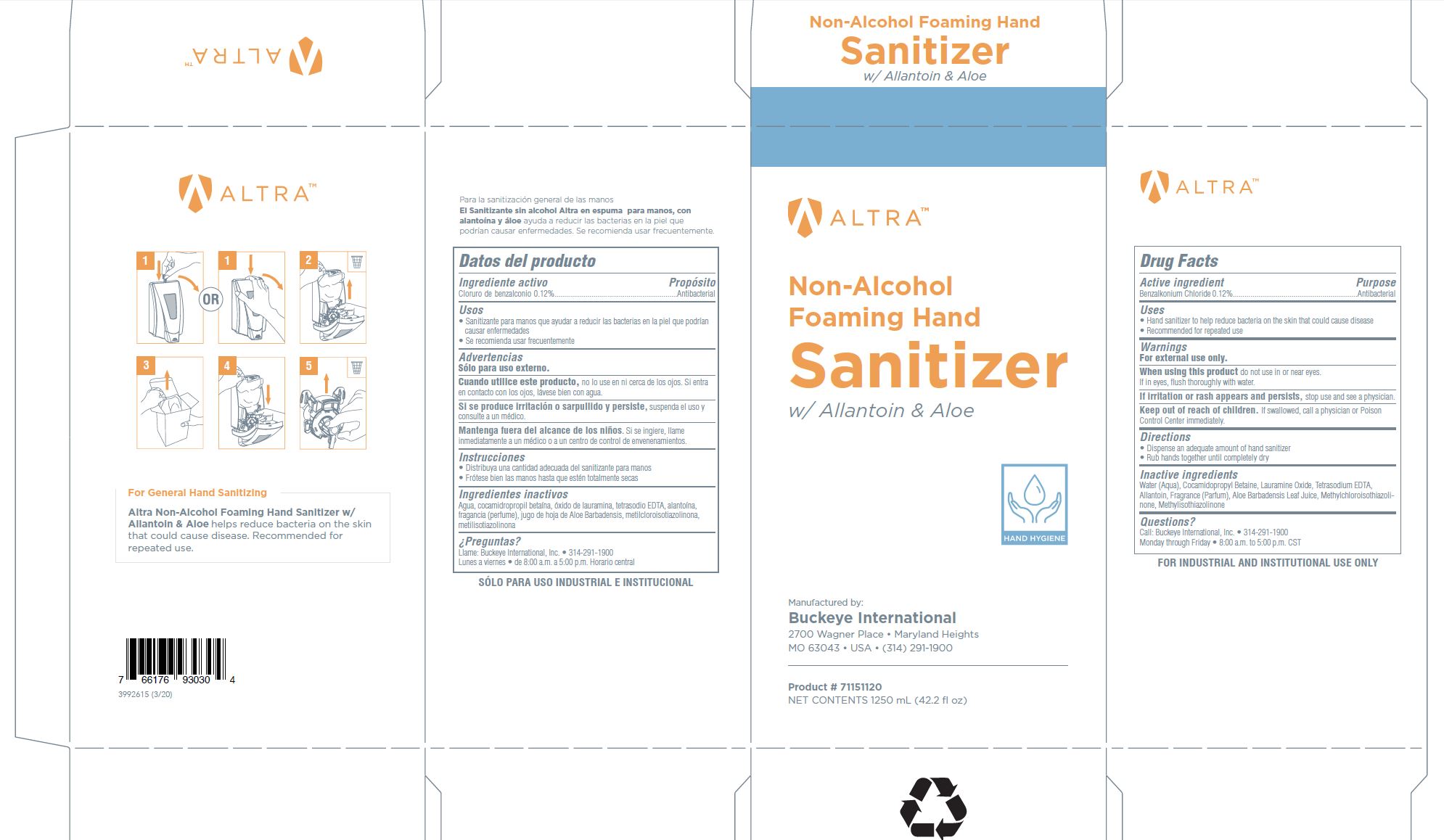 DRUG LABEL: Altra Non-Alcohol Foaming Hand Sanitizer with Allantoin and Aloe
NDC: 30805-015 | Form: SOLUTION
Manufacturer: Buckeye International, Inc.
Category: otc | Type: HUMAN OTC DRUG LABEL
Date: 20241115

ACTIVE INGREDIENTS: BENZALKONIUM CHLORIDE 0.12 g/100 mL
INACTIVE INGREDIENTS: METHYLCHLOROISOTHIAZOLINONE; LAURAMINE OXIDE; ALOE VERA LEAF; ALLANTOIN; COCAMIDOPROPYL BETAINE; WATER; EDETATE SODIUM; METHYLISOTHIAZOLINONE

Drug Facts 30805-015

Active ingredient

Benzalkonium Chloride 0.12%

Purpose

Antibacterial

Uses

- Hand sanitizer to help reduce bacteria on the skin that could cause disease
- Recommended for repeated use

Warnings

For external use only.

WHEN USING

When using this productdo not use in or near eyes.

If in eyes, flush thoroughly with water.

STOP USE

If irritation or rash appears and persists, stop use and see a physician.

Keep out of reach of children.

If swallowed, call a physician or Poison Control Center immediately.

Directions

- Dispense an adequate amount of hand sanitizer
- Rub hads together until completely dry

Inactive ingredients

Water (Aqua), Cocamidopropyl Betaine, Lauramine Oxide, Tetrasodium EDTA, Allantoin, Fragrance (Parfum), Aloe Barbadensis Leaf Juice, Methylchloroisothiazolinone, Methylisothiazolinone

Questions?

Call Buckeye International, Inc. 314-291-1900

Monday through Friday 8:00 a.m. to 5:00 p.m. CST

PACKAGE LABEL

ALTRA

Non-Alcohol

Foaming hand

Sanitizer

with Allantoin and Aloe

Hand Hygiene

Manufactured by

Buckeye International

2700 Wagner Place Maryland Heights

MO 63043 USA (314) 291-1900

Product # 71151120

Net Contents 1250 mL (42.2 fl oz)